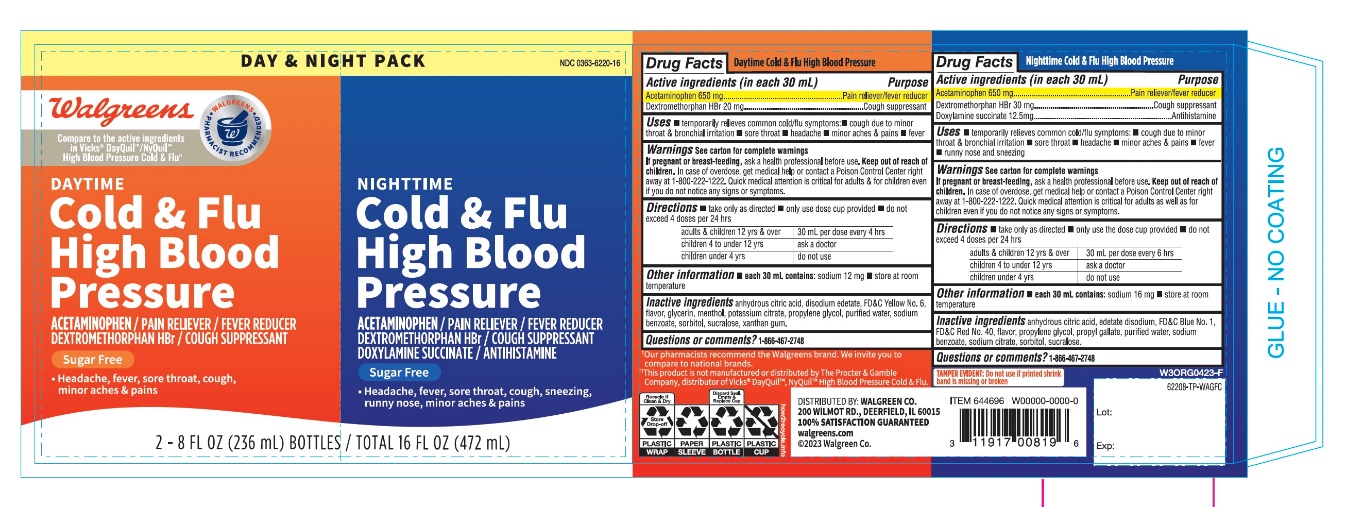 DRUG LABEL: WAG HBP Daytime and Nighttime

NDC: 0363-6220 | Form: KIT | Route: ORAL
Manufacturer: WALGREENS CO.
Category: otc | Type: HUMAN OTC DRUG LABEL
Date: 20251201

ACTIVE INGREDIENTS: ACETAMINOPHEN 650 mg/30 mL; DEXTROMETHORPHAN HYDROBROMIDE 20 mg/30 mL; ACETAMINOPHEN 650 mg/30 mL; DEXTROMETHORPHAN HYDROBROMIDE 30 mg/30 mL; DOXYLAMINE SUCCINATE 12.5 mg/30 mL
INACTIVE INGREDIENTS: ANHYDROUS CITRIC ACID; EDETATE DISODIUM; FD&C YELLOW NO. 6; GLYCERIN; MENTHOL, UNSPECIFIED FORM; POTASSIUM CITRATE; PROPYLENE GLYCOL; WATER; SODIUM BENZOATE; SORBITOL; SUCRALOSE; XANTHAN GUM; ANHYDROUS CITRIC ACID; EDETATE DISODIUM; FD&C BLUE NO. 1; FD&C RED NO. 40; PROPYLENE GLYCOL; PROPYL GALLATE; WATER; SODIUM BENZOATE; SODIUM CITRATE, UNSPECIFIED FORM; SORBITOL; SUCRALOSE

Walgreen HBP Nighttime and Daytime Cold & Flu Value Pack

HBP Nighttime Cold & Flu

Drug Facts

Active ingredients (in each 30 mL)

Acetaminophen 650 mg
Dextromethorphan HBr 30 mg
Doxylamine succinate 12.5 mg

PURPOSE

Pain reliever/ fever reducer
Cough suppressant
Antihistamine

Uses

temporarily relieves common cold/flu symptoms:

- cough due to minor throat & bronchial irritation
- sore throat
- headache
- minor aches & pains
- fever
- runny nose and sneezing

Warnings

See carton for complete warnings

PREGNANCY OR BREAST FEEDING

If pregnant or breast-feeding,ask a health professional before use.

Keep out of reach of children.

Overdose warning

In case of overdose, get medical help or contact a Poison Control Center right away 1-800-222-1222. Quick medical attention is critical for adults as well as for children even if you do not notice any signs or symptoms.

Directions

- take only as directed
- only use the dose cup provided
- do not exceed 4 doses per 24 hrs

adults & children 12 yrs & over | 30 mL every 6 hrs
children 4 to under 12 yrs | ask a doctor
children under 4 yrs | do not use

Other information

- each 30 mL contains:sodium 16 mg
- store at room temperature

Inactive ingredients

Anhydrous citric acid, edetate disodium, FD&C Blue No. 1, FD&C Red No. 40, flavor, propylene glycol, Propyl gallate, purified water, sodium benzoate, sodium citrate, sorbitol, sucralose

Questions?

1-866-467-2748

Distributed by:

HBPDaytime Cold & Flu Relief

Drug Facts

Active ingredients (in each 30 mL)

Acetaminophen 650 mg
Dextromethorphan HBr 20 mg

Purpose

Pain reliever/Fever reducer
Cough suppressant

Uses

temporarily relieves common cold/flu symptoms:

- nasal congestion
- cough due to minor throat & bronchial irritation
- sore throat
- headache
- minor aches & pains
- fever

Warnings

See carton for complete warnings

PREGNANCY OR BREAST FEEDING

If pregnant or breast-feeding,ask a health professional before use.

Keep out of reach of children.

Overdose warning

In case of overdose, get medical help or contact a Poison Control Center right away at1-800-222-1222. Quick medical attention is critical for adults as well as for children even if you do not notice any signs or symptoms.

Directions

- take only as directed
- only use the dose cup provided
- do not exceed 4 doses per 24 hrs

adults & children 12 yrs & over | 30 mL every 4 hrs
children 4 to under 12 yrs | ask a doctor
children under 4 yrs | do not use

Other information

- each 15 mL contains: sodium 46 mg
- store at room temperature and do not refrigerate.

Inactive ingredients

Anhydrous citric acid, disodium edetate, FD&C Yellow No. 6, flavor, glycerin, menthol, potassium citrate, propylene glycol, purified water, , sodium benzoate, sorbitol, sucralose

Questions?

1-866-467-2748

PRINCIPAL DISPLAY PANEL - Kit Carton

VALUE PACK

High Blood Pressure

Daytime

COLD & FLU

Acetaminophen ,Dextromethorphan HBr

- Headache, Fever, Sore Throat
- Minor Aches & Pains
- Cough

Daytime 8 FL OZ (236 ml) BOTTLE

High Blood Pressure

Nighttime

COLD & FLU

Nighttime Relief

Acetaminophen ,Doxylamine Succinate, Dextromethorphan HBr

- Headache, Fever, Sore Throat
- Minor Aches & Pains
- Sneezing, Runny Nose
- Cough

Sugar Free & No Added Alcohol

Nighttime 8 FL OZ (236 ml) BOTTLE

TOTAL 16 FL OZ (472 ml)